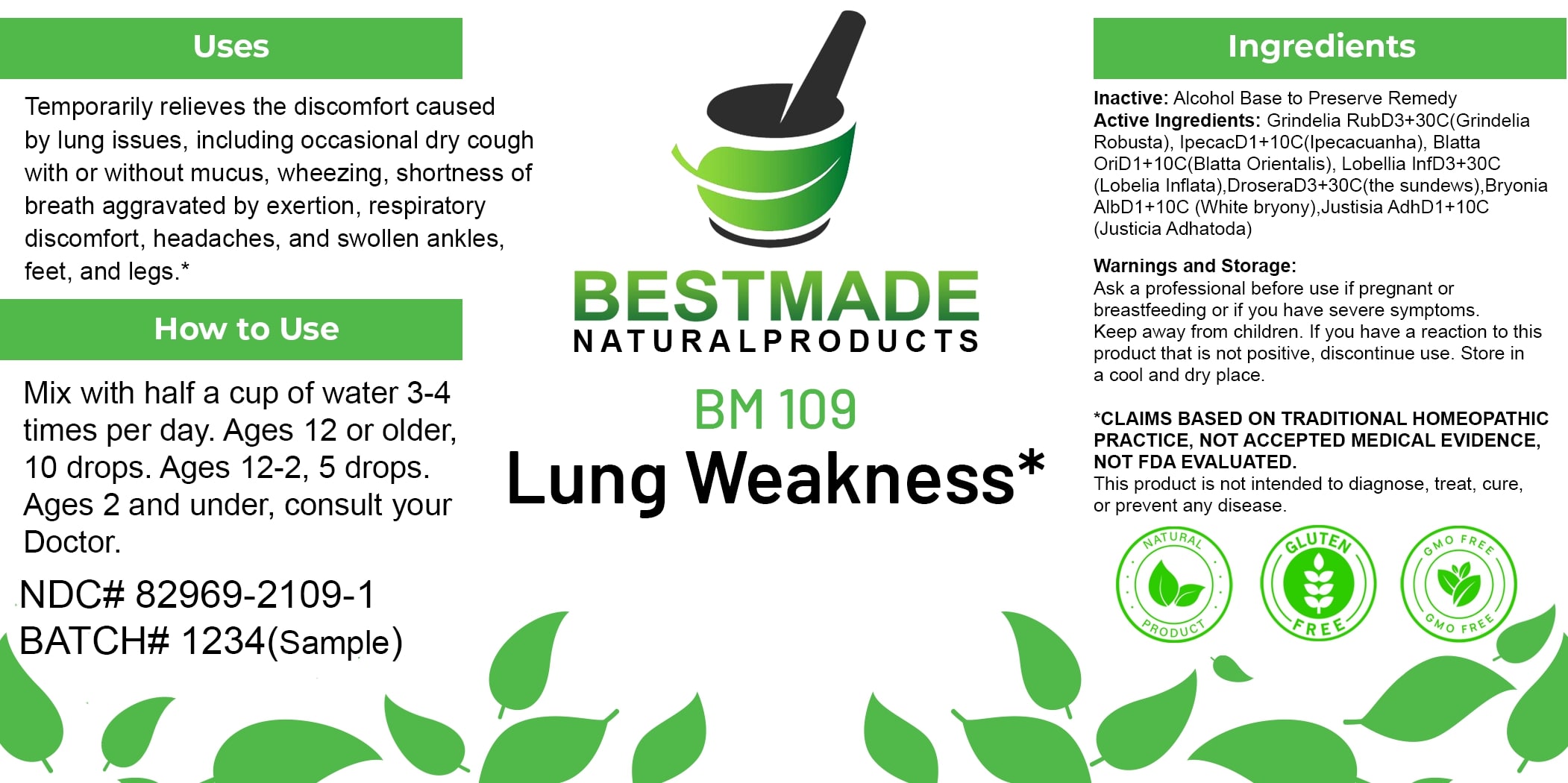 DRUG LABEL: Bestmade Natural Products BM109
NDC: 82969-2109 | Form: LIQUID
Manufacturer: Bestmade Natural Products
Category: homeopathic | Type: HUMAN OTC DRUG LABEL
Date: 20250207

ACTIVE INGREDIENTS: DROSERA ROTUNDIFOLIA 30 [hp_C]/30 [hp_C]; GRINDELIA HIRSUTULA WHOLE 30 [hp_C]/30 [hp_C]; BRYONIA ALBA ROOT 30 [hp_C]/30 [hp_C]; JUSTICIA ADHATODA LEAF 30 [hp_C]/30 [hp_C]; IPECAC 30 [hp_C]/30 [hp_C]; BLATTA ORIENTALIS 30 [hp_C]/30 [hp_C]; LOBELIA INFLATA 30 [hp_C]/30 [hp_C]
INACTIVE INGREDIENTS: ALCOHOL 30 [hp_C]/30 [hp_C]

BM109

DOSAGE AND ADMINISTRATION

How to Use

Mix with half a cup of water 3-4 times per day. Ages 12 or older, 10 drops. Ages 12-2, 5 drops. Ages 2 and under, consult your Doctor.

INACTIVE INGREDIENT

Ingredients

Inactive: Alcohol Base to Preserve Remedy

ACTIVE INGREDIENT

Active Ingredients: Grindelia RubD3+30C(Grindelia Robusta), IpecacD1+10C(Ipecacuanha), Blatta OriD1+10C(Blatta Orientalis), Lobelia InfD3+30C (Lobelia Inflata), DroseraD3+30C(the sundews), Bryonia AlbD1+10C (White bryony), Justicia AdhD1+10C (Justicia Adhatoda)

Uses

Temporarily relieves the discomfort caused by lung issues, including occasional dry cough with or without mucus, wheezing, shortness of breath aggravated by exertion, respiratory discomfort, headaches, and swollen ankles, feet, and legs.*

*CLAIMS BASED ON TRADITIONAL HOMEOPATHIC PRACTICE, NOT ACCEPTED MEDICAL EVIDENCE. NOT FDA EVALUATED.

This product is not intended to diagnose, treat, cure, or prevent any disease.

Uses

Temporarily relieves the discomfort caused by lung issues, including occasional dry cough with or without mucus, wheezing, shortness of breath aggravated by exertion, respiratory discomfort, headaches, and swollen ankles, feet, and legs.*

*CLAIMS BASED ON TRADITIONAL HOMEOPATHIC PRACTICE, NOT ACCEPTED MEDICAL EVIDENCE. NOT FDA EVALUATED.

This product is not intended to diagnose, treat, cure, or prevent any disease.

KEEP OUT OF REACH OF CHILDREN

Warnings and Storage:

Ask a professional before use if pregnant or breastfeeding or if you have severe symptoms. Keep away from children. If you have a reaction to this product that is not positive, discontinue use. Store in a cool and dry place.

Warnings and Storage:

Ask a professional before use if pregnant or breastfeeding or if you have severe symptoms. Keep away from children. If you have a reaction to this product that is not positive, discontinue use. Store in a cool and dry place.

*CLAIMS BASED ON TRADITIONAL HOMEOPATHIC PRACTICE, NOT ACCEPTED MEDICAL EVIDENCE. NOT FDA EVALUATED.

This product is not intended to diagnose, treat, cure, or prevent any disease.

Entire package label